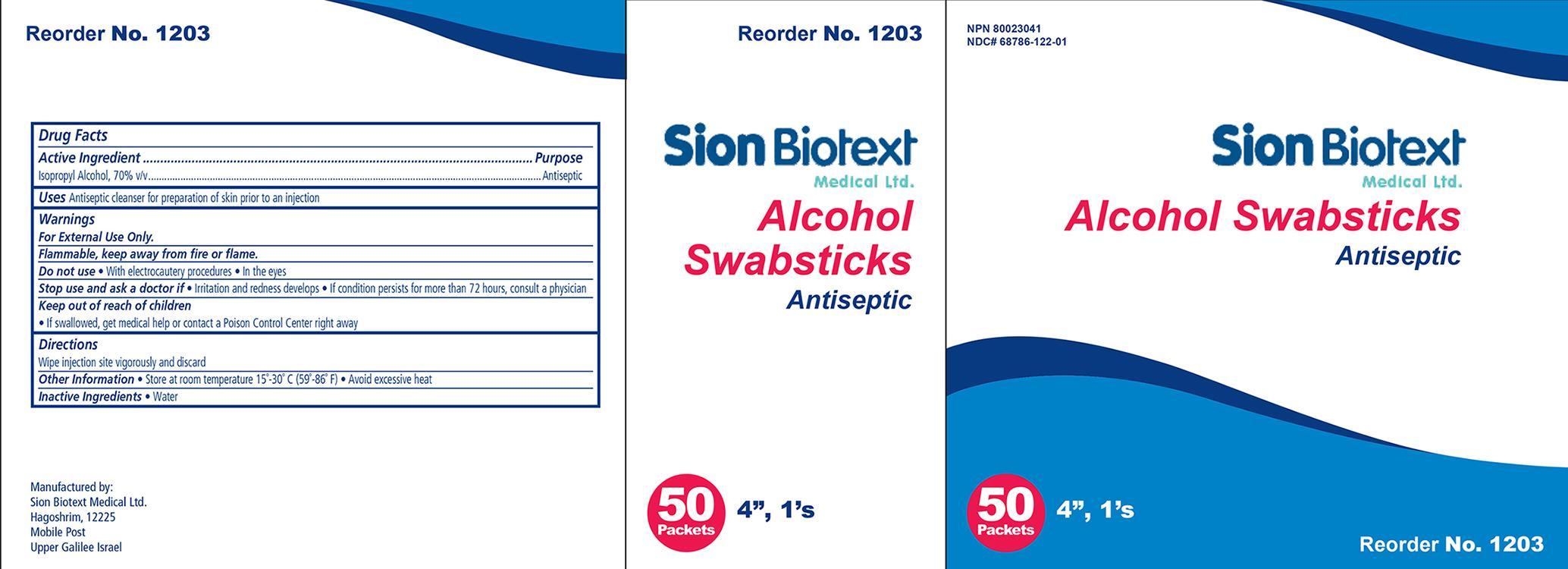 DRUG LABEL: alcohol
NDC: 68786-122 | Form: SWAB
Manufacturer: Sion Biotext Medical Ltd
Category: otc | Type: HUMAN OTC DRUG LABEL
Date: 20240124

ACTIVE INGREDIENTS: ISOPROPYL ALCOHOL 0.7 mL/1 mL
INACTIVE INGREDIENTS: WATER

Sion Biotext Medical Alcohol Swabstick

Active Ingredient Purpose

Isopropyl Alcohol 70% v/v Antiseptic

Uses: alcohol

- Antiseptic cleanser.

Warnings:

- FOR EXTERNAL USE ONLY

Do not use:

- In the eyes.
- With electrocautery procedures.

Stop use and ask a doctor:

- If irritation and redness develop
- If condition persists for more than 72 hours, consult a physician.

Keep out of reach of children.If swallowed, get medical help or contact a Poison Control Center.

Directions:

Tear at notch, remove swab, use only once.

- Wipe injection site vigorously and discard.

Inactive Ingredient

Inactive Ingredient: Water

Indications and Usage:

For use as an

- antiseptic

Principal Display Panel

Sion Biotext medical Alcohol Swabstick

Sion Swabstick.jpg